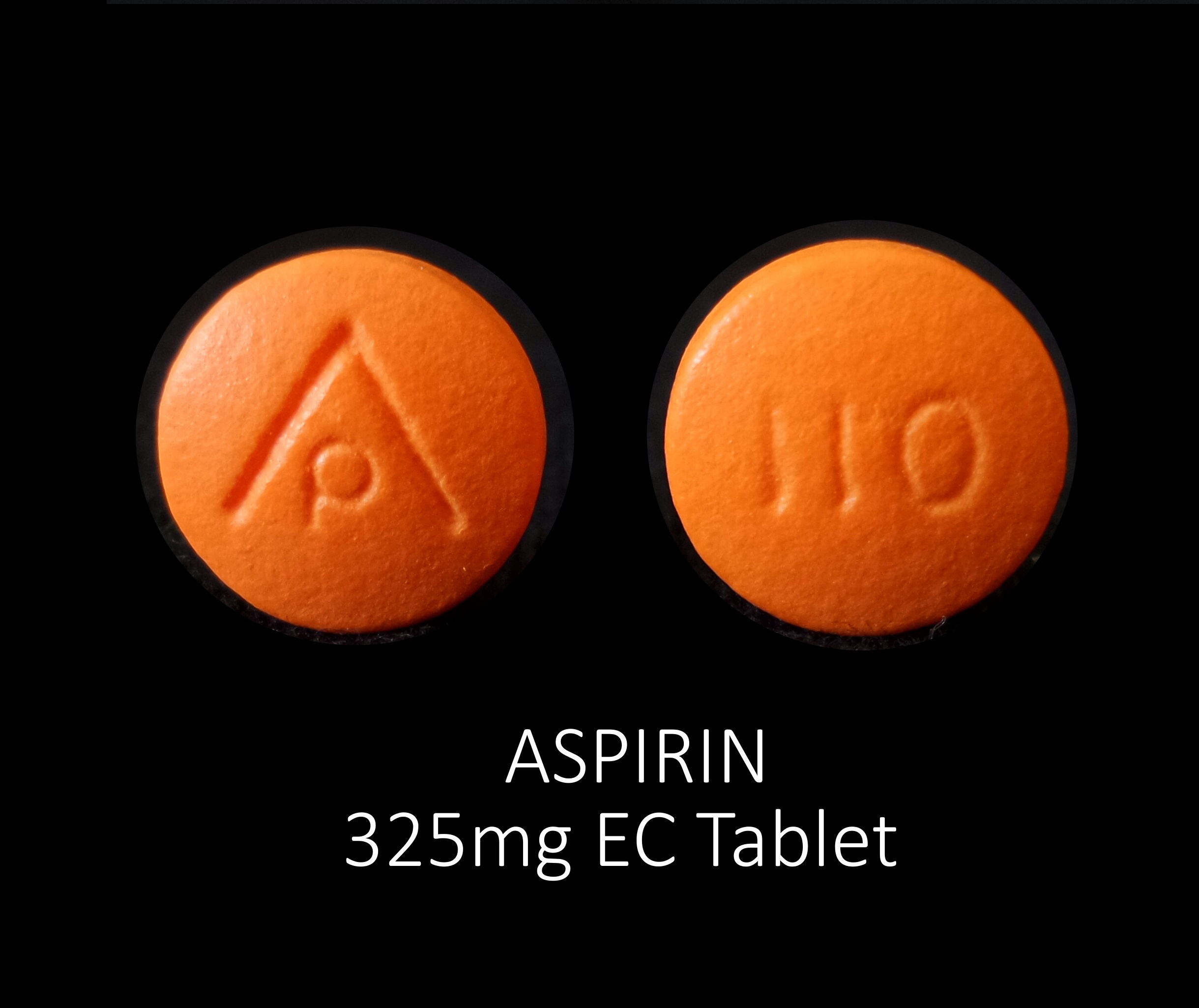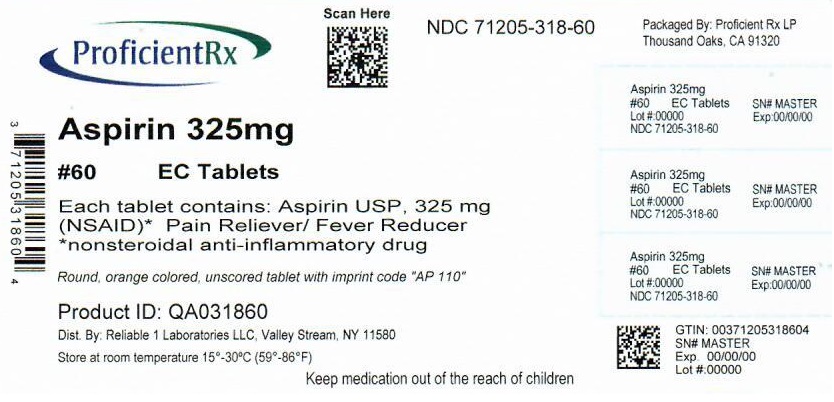 DRUG LABEL: ASPIRIN 325 MG EC
NDC: 71205-318 | Form: TABLET
Manufacturer: Proficient Rx LP
Category: otc | Type: HUMAN OTC DRUG LABEL
Date: 20251001

ACTIVE INGREDIENTS: ASPIRIN 325 mg/1 1
INACTIVE INGREDIENTS: POVIDONE, UNSPECIFIED; METHACRYLIC ACID; STEARIC ACID; STARCH, CORN; CROSCARMELLOSE SODIUM; FD&C YELLOW NO. 6; D&C YELLOW NO. 10; HYPROMELLOSE, UNSPECIFIED; PROPYLENE GLYCOL; TITANIUM DIOXIDE; TALC; SODIUM LAURYL SULFATE; POLYETHYLENE GLYCOL 1000

ASPIRIN 325 MG EC TABLET

Drug Facts

ACTIVE INGREDIENT

Aspirin USP, 325 mg (NSAID)*

*nonsteroidal anti-inflammatory drug

PURPOSE

Pain Reliever/Fever Reducer

INDICATIONS AND USAGE

temporarily relieves

- headache
- menstrual pain
- minor pain of arthritis
- muscle pain
- toothache
- pain and fever of colds

Warnings

Reye's syndrome: Children and teenagers who have or are recovering from chicken pox or flu-like symptoms should not use this product. When using this prodcut, if changes in behavior with nausea and vomiting occur, consult a doctor because these symptoms could be an early sign of Reye's syndrome, a rare but serious illness.

Allergy alert: Aspirin may cause a severe allergic reaction which may include

- hives
- facial swelling
- asthma (wheezing)
- shock

OTHER SAFETY INFORMATION

Stomach bleeding warning: This prodcut contains an NSAID, which may cause severe stomach bleeding. The chance is higher if you

- are age 60 or older
- have had stomach ulcers or bleeding problems
- take a blood thinning (anticoagulant) or steroid drug
- take other drugs containing prescription or nonprescription NSAIDs (ibuprofen, naproxen, or others)
- take more or for a longer time than directed
- have 3 or more alcoholic drinks every day while using this product

Drug Facts continued on back of label

Do not use if you have ever had an allergic reaction to any other pain reliever/fever reducer

Ask a doctor before use if

- stomach bleeding warning applies to you
- you have a history of stomach problems, such as heartburn
- you have high blood pressure, heart disease, liver cirrhosis, or kidney disease
- you are taking a diuretic
- you have asthma

Ask a doctor or pharmacist before use if you are

- taking a prescription drug for diabetes, gout or arthritis
- under a doctor's care for any serious condition
- taking any other drug

Stop use and ask a doctor if

- you experience any of the following signs of stomach bleeding:

• feel faint

• vomit blood

• have bloody or black stools

• have stomach pain that does not get better

- pain gets worse or lasts more than 10 days
- fever gets worse or lasta more than 3 days
- redness or swelling is present in the painful area
- any new symptoms appear
- ringing in the ears or loss of hearing occurs

These could be sings of a serious condition

PREGNANCY OR BREAST FEEDING

If pregnant or breast-feeding, ask a health professional before use. It is especially imporant not to use aspirin during the last 3 months of pregnancy unless definitely directed to do so by a doctor because it may cause problems in the unborn child or complications during delivery.

Keep out of reach of children. In case of overdose, get medical help or contact a Poison Control Center right away.

Directions

DRINK A FULL GLASS OF WATER WITH EACH DOSE

- adults and children 12 years and over: 1-2 tablets every 4 hours while symptoms last, not more than 12 tablets in 24 hours
- children under 12 years: ask a doctor

Other information

- store at room temperature 15°-30ºC (59°-86°F)

Inactive ingredients

croscarmellose sodium, D&C yellow #10 (Al-lake), FD&C yellow #6 (Al-lake), HPMC, methacrylic acid copolymer, polyethylene glycol, propylene glycol, povidone, sodium lauryl sulfate, starch, stearic acid, talc, titanium dioxide

Questions or comments ? call 516-341-0666, 8:30 am - 4:30 pm ET, Monday - Friday

TAMPER EVIDENT: DO NOT USE IF IMPRINTED SAFETY SEAL UNDER CAP IS BROKEN OR MISSING

*Reliable 1 Laboratories LLC is not affiliated with the owner of the trademark Ecotrin®.

Distributed by: Reliable 1 Laboratories LLC, Valley Stream, NY 11580

Repackaged by: Proficient Rx LP Thousand Oaks, CA 91320

www.reliable1labs.com

PACKAGE LABEL

NDC 71205-318-60

Enteric Coated

Aspirin USP 325 mg (NSAID)

PAIN RELIEVER

FEVER REDUCER

60 TABLETS

*Compare to Active Ingredients in Ecotrin®